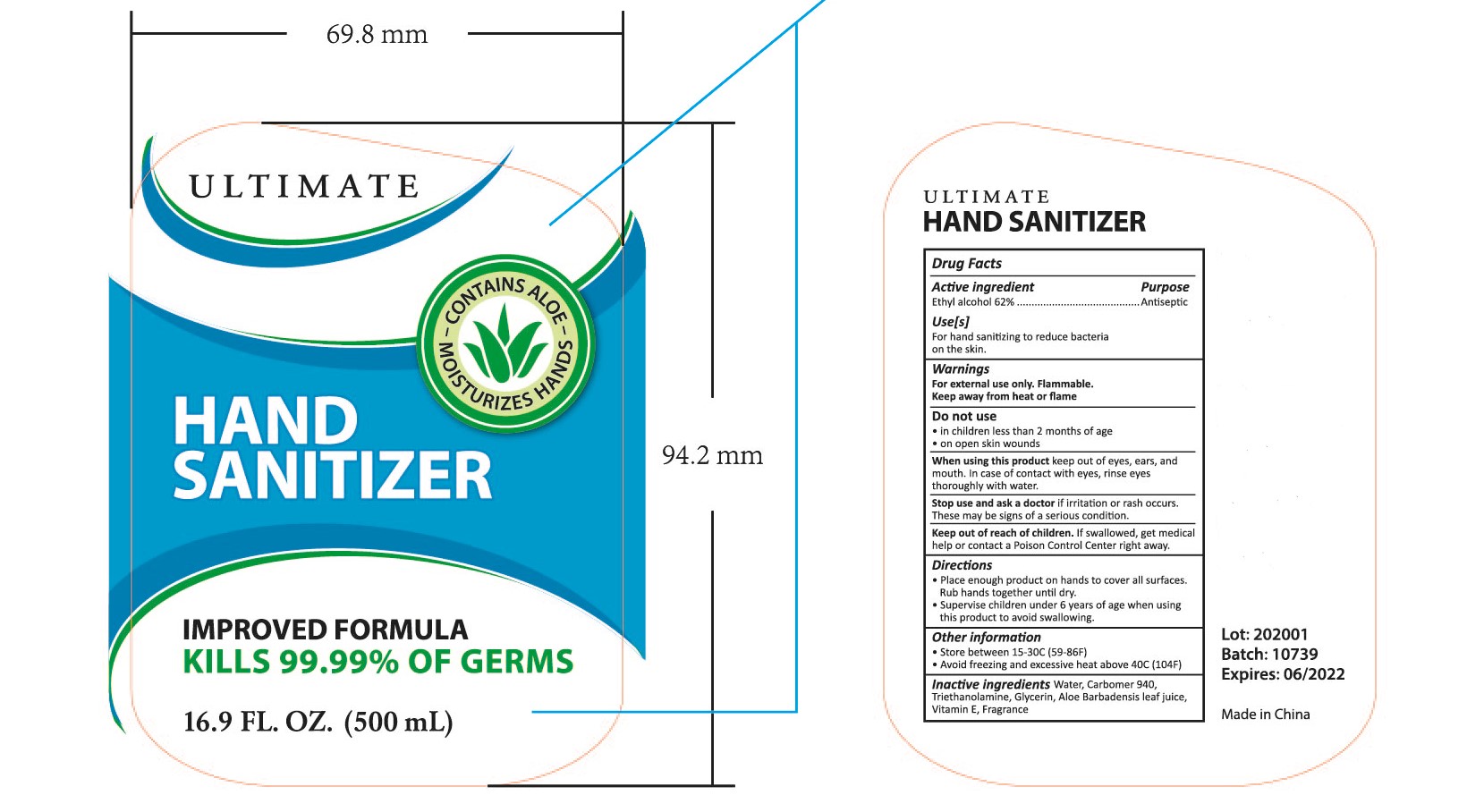 DRUG LABEL: HAND SANITIZER
NDC: 47993-223 | Form: GEL
Manufacturer: NINGBO JIANGBEI OCEAN STAR TRADING CO.,LTD
Category: otc | Type: HUMAN OTC DRUG LABEL
Date: 20201103

ACTIVE INGREDIENTS: ALCOHOL 62 g/112 mL
INACTIVE INGREDIENTS: CARBOMER 940 12 g/112 mL; TRIETHANOLAMINE BENZOATE 3 g/112 mL; ALOE VERA LEAF 1 g/112 mL; WATER 19.3 g/112 mL; GLYCERIN 2 g/112 mL; TOCOPHEROL 0.5 g/112 mL

47993-223

Active ingredients

Ethyl Alcohol 62%

PURPOSE

Active ingredients

Ethyl Alcohol 62%

Warnings:

For external use only.Flammable.

Keep away from heat or flame.

Do not use

in children less than 2 months of age.
on open skin wounds

When using this product

keep out of eyes，ears and mouth. In case of contact with eyes，rinse eyes thoroughly with water.

Stop use and ask a doctor

If irritation or rash occurs. These may be signs of a serious condition.

Keep out of reach of children.

If swallowed,get medical help or contact a Poison Control Center right away.

Uses：

For hand sanitizing to reduce bacteria on the skin.

Directions:

Place enough product on hands to cover all surfaces,Rub hands together until dry.
Supervise children under 6 years of age when using this product to avoid swallowing.

OTHER SAFETY INFORMATION

Store between 15-30℃（59-86℉）
Avoid freezing and excessive heat above 40 ℃（104℉）

Inactive Ingredients:

Water,Carbomer 940,Triethanolamine,Glycerin,Aloe barbadensis leaf juice,Vitamin E,Fragrance